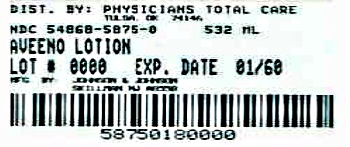 DRUG LABEL: Aveeno
NDC: 54868-5875 | Form: LOTION
Manufacturer: Physicians Total Care, Inc.
Category: otc | Type: HUMAN OTC DRUG LABEL
Date: 20120521

ACTIVE INGREDIENTS: Dimethicone 13 mg/1 g
INACTIVE INGREDIENTS: AVENA SATIVA FLOWERING TOP; Benzyl Alcohol; Cetyl Alcohol; Distearyldimonium Chloride; Glycerin; Isopropyl Palmitate; Petrolatum; Sodium Chloride; Water

Aveeno®
Active Naturals™
Daily Moisturizing
LOTION

Drug Facts

Active ingredient

Dimethicone 1.25%

Purposes

Skin Protectant

Uses

- Helps prevent and temporarily protects chafed, chapped, or cracked skin

Warnings

For external use only.

When using this product

- Do not get into eyes

Stop use and ask a doctor if

- Condition worsens
- Symptoms last more than 7 days or clear up and occur again within a few days.

Keep out of reach of children. If swallowed, get medical help or contact a Poison Control Center immediately.

Directions

- Apply liberally as often as needed.

Inactive ingredients

Avena Sativa (Oat) Kernel flour, Benzyl Alcohol, Cetyl Alcohol, Distearyldimonium Chloride, Glycerin, Isopropyl Palmitate, Petrolatum, Sodium Chloride, Water

Questions?

1-877-288-2525 or visit www.Aveeno.com

PRINCIPAL DISPLAY PANEL

dermatologist
recommended

Aveeno®
ACTIVE NATURALS®

Daily Moisturizing
LOTION
dimethicone skin protectant

clinically proven to
relieve dry skin

moisturizes for 24 hours
fragrance free

with
natural colloidal oatmeal

18 fl. oz. (532 mL)

NDC 54868-5875-0

Additional barcode labeling by:
Physicians Total Care, Inc.
Tulsa, Oklahoma 74146